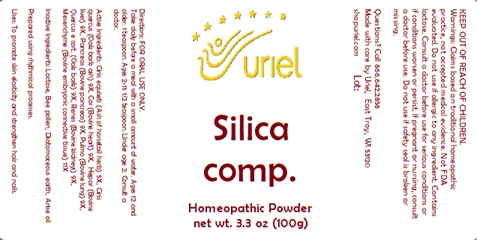 DRUG LABEL: Silica comp.
NDC: 48951-8327 | Form: POWDER
Manufacturer: Uriel Pharmacy Inc.
Category: homeopathic | Type: HUMAN OTC DRUG LABEL
Date: 20241205

ACTIVE INGREDIENTS: EQUISETUM ARVENSE TOP 5 [hp_X]/1 g; QUERCUS ROBUR WHOLE 9 [hp_X]/1 g; BEEF HEART 9 [hp_X]/1 g; MAMMAL LIVER 9 [hp_X]/1 g; SUS SCROFA PANCREAS 9 [hp_X]/1 g; SUS SCROFA LUNG 9 [hp_X]/1 g; PORK KIDNEY 9 [hp_X]/1 g; BOS TAURUS CARTILAGE 11 [hp_X]/1 g
INACTIVE INGREDIENTS: BEE POLLEN; DIATOMACEOUS EARTH; LACTOSE, UNSPECIFIED FORM; ANISE OIL

Silica comp.

INDICATIONS AND USAGE

Directions: FOR ORAL USE ONLY.

DOSAGE AND ADMINISTRATION

Take regularly before meals with a small amount of water. Ages 12 and older: 1 teaspoon. Ages 2-11: 1/2 teaspoon. Under age 2: Consult a doctor.

ACTIVE INGREDIENT

Active Ingredients: Cinis equiseti (Ash of horsetail herb) 5X, Cinis quercus (Oak bark ash) 9X, Cor (Bovine heart) 9X, Hepar (Bovine liver) 9X, Pancreas (Bovine pancreas) 9X, Pulmo (Bovine lung) 9X, Quercus e cort. (Oak bark) 9X, Renes (Porcine kidneys) 9X, Mesenchyme (Bovine embryonic connective tissue) 11X

INACTIVE INGREDIENT

Inactive Ingredients: Lactose, Bee pollen, Diatomaceous earth, Anise oil

Prepared using rhythmical processes.

PURPOSE

Uses: To promote skin elasticity and strengthen hair and nails.

KEEP OUT OF REACH OF CHILDREN.

WARNINGS

Warnings: Claims based on traditional homeopathic practice, not accepted medical evidence. Not FDA evaluated. Do not use if allergic to any ingredient. Contains lactose. Consult a doctor before use for serious conditions or if conditions worsen or persist. If pregnant or nursing, consult a doctor before use. Do not use if safety seal is broken or missing.

Questions? Call 866.642.2858
Made with care by Uriel, East Troy, WI 53120
shopuriel.com Lot: